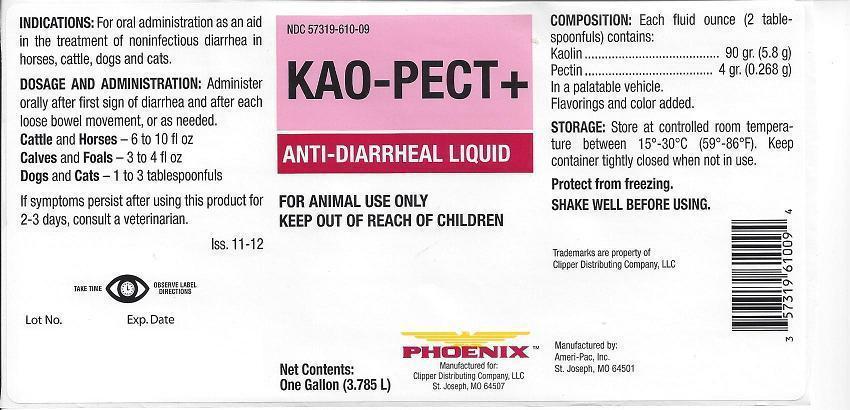 DRUG LABEL: Kao-Pect Plus
NDC: 57319-610 | Form: SUSPENSION
Manufacturer: Phoenix Pharmaceutical Inc./ Clipper Distributing, Inc.
Category: animal | Type: OTC ANIMAL DRUG LABEL
Date: 20130916

ACTIVE INGREDIENTS: KAOLIN 196 mg/1 mL; PECTIN, CITRUS 9 mg/1 mL
INACTIVE INGREDIENTS: GUAR GUM; METHYLPARABEN; POTASSIUM SORBATE; SACCHARIN SODIUM; PROPYLPARABEN; FD&C RED NO. 40

KAO-PECT+ Anti-Diarrheal Liquid

NDC 57319-610-09 KAO-PECT + ANTI-DIARRHEAL LIQUID FOR ANIMAL USE ONLY KEEP OUT OF REACH OF CHILDREN

Net Contents:

One Gallon (3.785L)

PHOENIX TM

Manufactured for:

Clippker Distributing Company,, LLC

St Joseph, MO 64507

INDICATIONS:

For oral administration as an aid in the treatment of noninfectious diarrhea in horses, cattle, dogs and cats.

DOSAGE AND ADMINISTRATION:

Administer orally after first sign of diarrhea and after each loose bowel movement or as needed.

Cattle and Horses - 6 to 10 fl oz

Calves and Foals - 3 to 4 fl oz

Dogs and Cats - 1 to 3 tablespoonfuls

If symptons persist after using this product for 2-3 days, consult a veterinarian.

Iss. 11-12

WARNINGS

TAKE TIME OBSERVE LABEL DIRECTIONS

Lot No. Exp. Date

COMPOSITION:

Each fluid ounce (2 tablespoonfuls) contains:

Kaolin ........ 90 gr. (5.8 g)

Pectin ......... 4 gr. (0.268 g)

In a palatable vehicle.

Flavorings and color added.

STORAGE:

Store at controlled room temperature between 15º-30ºC (59º-86ºF). Keep container tightly closed when not in use.

Protect from freezing

SHAKE WELL BEFORE USING

Trademarks are property of

Clipper Distributing Company, LLC

Manufactured by:

Ameri-Pac, Inc.

St. Joseph, MO 64501